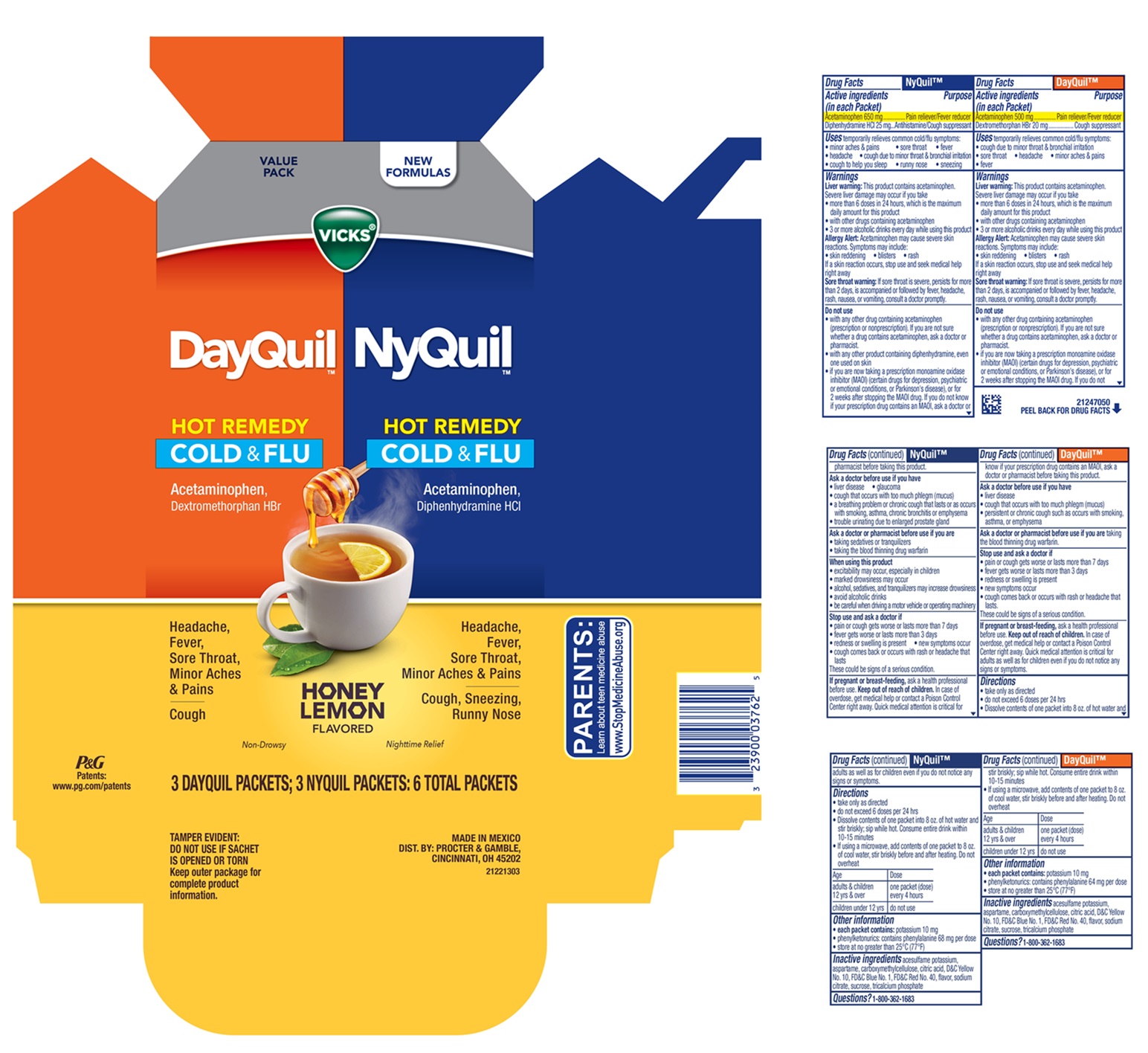 DRUG LABEL: Vicks DayQuil NyQuil HOT REMEDY
NDC: 58933-556 | Form: KIT | Route: ORAL
Manufacturer: Procter & Gamble Manufactura S de RL de CV
Category: otc | Type: HUMAN OTC DRUG LABEL
Date: 20251208

ACTIVE INGREDIENTS: DIPHENHYDRAMINE HYDROCHLORIDE 25 mg/1 1; ACETAMINOPHEN 650 mg/1 1; DEXTROMETHORPHAN HYDROBROMIDE 20 mg/5 g; ACETAMINOPHEN 500 mg/5 g
INACTIVE INGREDIENTS: ACESULFAME POTASSIUM; ANHYDROUS CITRIC ACID; TRISODIUM CITRATE DIHYDRATE; D&C YELLOW NO. 10; TRICALCIUM PHOSPHATE; SUCROSE; ASPARTAME; FD&C BLUE NO. 1; FD&C RED NO. 40; CARBOXYMETHYLCELLULOSE; TRISODIUM CITRATE DIHYDRATE; SUCROSE; TRICALCIUM PHOSPHATE; CARBOXYMETHYLCELLULOSE; FD&C BLUE NO. 1; D&C YELLOW NO. 10; ACESULFAME POTASSIUM; FD&C RED NO. 40; ASPARTAME; ANHYDROUS CITRIC ACID

Vicks@DayQuil™ HOT REMEDY Vicks®NyQuil™ HOT REMEDY
COLD & FLU

Vicks® DayQuil™ HOT REMEDY COLD & FLU

Drug Facts

DayQuil™

Active Ingredient (in each Packet)

Acetaminophen 500 mg

Dextromethorphan HBr 20 mg

Purpose

Headache, Fever, Sore Throat, Minor Aches & Pains

Cough

Uses

temporarily relieves common cold/flu symptoms:

- cough due to minor throat & bronchial irritation
- sore throat
- headache
- minor aches & pains
- fever

Liver warning:

This product contains acetaminophen. Severe liver damage may occur if you take

- more than 6 doses in 24 hours, which is the maximum daily amount for this product
- with other drugs containing acetaminophen
- 3 or more alcoholic drinks every day while using this product

Allergy Alert:

Acetaminophen may cause severe skin reactions. Symptoms may include:

- Skin reddening
- Blisters
- Rash

If a skin reaction occurs, stop use and seek medical help right away

Sore throat warning:

If sore throat is severe, persists for more than 2 days, is accompanied or followed by fever, headache, rash, nausea, or vomiting, consult a doctor promptly.

Do not use

• with any other drug containing acetaminophen (prescription or nonprescription). If you are not sure whether a drug contains acetaminophen, ask a doctor or pharmacist.

• if you are now taking a prescription monoamine oxidase inhibitor (MAOI) (certain drugs for depression, psychiatric or emotional conditions, or Parkinson's disease), or for 2 weeks after stopping the MAOI drug. If you do not know if your prescription drug contains an MAOI, ask a doctor or pharmacist before taking this product.

Ask a doctor before use if you have

- liver disease
- cough that occurs with too much phlegm (mucus)
- persistent or chronic cough such as occurs with smoking, asthma, or emphysema

Ask a doctor or pharmacist before use if you are

taking the blood thinning drug warfarin

Stop use and ask a doctor if

- pain or cough gets worse or lasts more than 7 days
- fever gets worse or lasts more than 3 days
- redness or swelling is present
- new symptoms occur
- cough comes back or occurs with rash or headache that lasts.

These could be signs of a serious condition.

In case of overdose, get medical help or contact a Poison Control Center right away. Quick medical attention is critical for adults as well as for children even if you do not notice any signs or symptoms.

Directions

- take only as directed
- do not exceed 6 doses per 24 hrs
- Dissolve contents of one packet into 8 oz. of hot water and stir briskly; sip while hot. Consume entire drink within 10-15 minutes
- If using a microwave, add contents of one packet to 8 oz. of cool water, stir briskly before and after heating. Do not overheat

Age | Dose
adults & children 12 yrs & over | one packet (dose) every 4 hours
children under 12 yrs | do not use

Other information

- each packet contains: potassium 10 mg
- phenylketonurics: contains phenylalanine 68 mg per dose
- store at no greater than 25°C (77°F)

Inactive ingredients:

acesulfame potassium, aspartame, carboxymethylcellulose, citric acid, D&C Yellow No. 10, FD&C Blue No. 1, FD&C Red No. 40, flavor, sodium citrate, sucrose, tricalcium phosphate

Questions?

1-800-362-1683

MADE IN MEXICO

DIST. BY PROCTER & GAMBLE,
CINCINNATI OH 45202

Vicks® NyQuil™ HOT REMEDY COLD & FLU

Drug Facts

NyQuil™

Active Ingredient (in each Packet)

Acetaminophen 650 mg

Diphenhydramine HCl 25 mg

Purpose

Pain reliever/fever reducer

Antihistamine/Cough suppressant

Nasal decongestant

Uses

temporarily relieves common cold/flu symptoms:

- minor aches & pains
- sore throat
- fever
- headache
- cough due to minor sore throat & bronchial irritation
- cough to help you sleep
- runny nose
- sneezing

Liver warning:

This product contains acetaminophen. Severe liver damage may occur if you take

- more than 6 doses in 24 hours, which is the maximum daily amount for this product
- with other drugs containing acetaminophen
- 3 or more alcoholic drinks every day while using this product

Allergy Alert:

Acetaminophen may cause severe skin reactions. Symptoms may include:

- Skin reddening
- Blisters
- Rash

If a skin reaction occurs, stop use and seek medical help right away

Sore throat warning:

If sore throat is severe, persists for more than 2 days, is accompanied or followed by fever, headache, rash, nausea, or vomiting, consult a doctor promptly.

Do not use

- with any other drug containing acetaminophen (prescription or nonprescription). If you are not sure whether a drug contains acetaminophen, ask a doctor or pharmacist.
- with any other product containing diphenhydramine, even one used on skin.
- if you are now taking a prescription monoamine oxidase inhibitor (MAOI) (Certain drugs for depression, psychiatric or emotional conditions, or Parkinson's disease), or for 2 weeks after stopping the MAOI drug. If you do not know if your prescription drug contains an MAOI, ask a doctor or pharmacist before taking this product.

Ask a doctor before use if you have

- liver disease
- glaucoma
- cough that occurs with too much phlegm (mucus)
- a breathing problem or chronic cough that lasts or as occurs with smoking, asthma, chronic bronchitis or emphysema
- trouble urinating due to enlarged prostate gland

Ask a doctor or pharmacist before use if you are

- taking sedatives or tranquilizers
- taking the blood thinning drug warfarin

When using this product

- excitability may occur especially in children
- marked drowsiness may occur
- alcohol, sedatives, and tranquilizers may increase drowsiness
- avoid alcoholic drinks
- be careful when driving a motor vehicle or operating machinery

Stop use and ask a doctor if

- pain or cough gets worse or lasts more than 7 days
- fever gets worse or lasts more than 3 days
- redness or swelling is present
- new symptoms occur
- cough comes back or occurs with rash or headache that lasts.

These could be signs of a serious condition.

If pregnant or breast-feeding,

ask a health professional before use.

Keep out of reach of children.

In case of overdose, get medical help or contact a Poison Control Center right away. Quick medical attention is critical for adults as well as for children even if you do not notice any signs or symptoms.

Directions

- take only as directed
- do not exceed 6 doses per 24 hrs
- Dissolve contents of one packet into 8 oz. of hot water and stir briskly; sip while hot. Consume entire drink within 10-15 minutes
- If using a microwave, add contents of one packet to 8 oz. of cool water, stir briskly before and after heating. Do not overheat

Age | Dose
adults & children 12 yrs & over | one packet (dose) every 4 hours
children under 12 yrs | do not use

Other information

• each packet contains:potassium 10 mg

- phenylketonurics: contains phenylalanine 68 mg per dose
- store at no greater than 25°C (77°F)

Inactive ingredients

acesulfame potassium, aspartame, carboxymethylcellulose, citric acid, D&C Yellow No. 10, FD&C Blue No. 1, FD&C Red No. 40, flavor, sodium citrate, sucrose, tricalcium phosphate

Questions?

1-800-362-1683

TAMPER EVIDENT: DO NOT USE IF SACHET IS OPENED OR TORN

Keep outer package for complete product information.

MADE IN MEXICO

DIST. BY PROCTER & GAMBLE,
CINCINNATI OH 45202

PRINCIPAL DISPLAY PANEL - 6 packet package

NEW FORMULAS

VALUE PACK

Vicks®DayQuil™ HOT REMEDY

COLD & FLU

Acetaminophen,Dextromethorphan HBr

Headache, Fever, Sore Throat, Minor Aches & Pains

Cough

Non-Drowsy

Vicks®NyQuil™ HOT REMEDY

COLD & FLU

Acetaminophen, Diphenhydramine HCl

Headache, Fever, Sore Throat, Minor Aches & Pains

Cough, Sneezing, Runny Nose

Nighttime Relief

HONEY LEMON FLAVORED

3 DAYQUIL PACKETS; 3 NYQUIL PACKETS; 6 TOTAL PACKETS